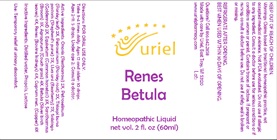 DRUG LABEL: Renes Betula
NDC: 48951-8125 | Form: LIQUID
Manufacturer: Uriel Pharmacy Inc.
Category: homeopathic | Type: HUMAN OTC DRUG LABEL
Date: 20210706

ACTIVE INGREDIENTS: ELYMUS REPENS ROOT 4 [hp_X]/1 mL; ONONIS REPENS ROOT 2 [hp_X]/1 mL; PARSLEY 2 [hp_X]/1 mL; CAPSELLA BURSA-PASTORIS 2 [hp_X]/1 mL; ARCTOSTAPHYLOS UVA-URSI LEAF 2 [hp_X]/1 mL; SOLIDAGO VIRGAUREA FLOWERING TOP 2 [hp_X]/1 mL; BETULA PUBESCENS LEAF 4 [hp_X]/1 mL; EQUISETUM ARVENSE TOP 3 [hp_X]/1 mL; PORK KIDNEY 6 [hp_X]/1 mL; CYTISUS SCOPARIUS FLOWERING TOP 3 [hp_X]/1 mL; COPPER 8 [hp_X]/1 mL; PETROSELINUM CRISPUM ROOT 2 [hp_X]/1 mL
INACTIVE INGREDIENTS: WATER; PROPOLIS WAX; LACTOSE

Renes Betula

INDICATIONS AND USAGE

Directions: FOR ORAL USE ONLY.

DOSAGE AND ADMINISTRATION

Take 3-4 times daily. Ages 12 and older: 10 drops. Ages 2-11: 5 drops. Under age 2: Consult a doctor.

ACTIVE INGREDIENT

Active Ingredients: Agropyron (Couch grass) 4X, Ononis (Restharrow) 2X, Petroselinum (Parsley leaf) 2X, Petroselinum (Parsley root) 2X, Thlaspi bursa pastoris (Shepherd’s purse) 2X, Uva ursi (Bearberry) 2X, Solidago (Goldenrod) 2X, Betula (Silver birch leaves) 4X, Equisetum (Common horsetail) 3X, Renes (Bovine kidneys) 6X, Sarothamnus (Broom) 3X, Cuprum met. (Copper) 8X

Inactive Ingredients: Distilled water, Propolis, Lactose

PURPOSE

Use: Temporary relief of urinary discomfort.

KEEP OUT OF REACH OF CHILDREN.

WARNINGS

Warnings: Claims based on traditional homeopathic practice, not accepted medical evidence. Not FDA evaluated. Do not use if allergic to any ingredient. Consult a doctor before use for serious conditions or if conditions worsen or persist. Contains traces of lactose. If pregnant or nursing, consult a doctor before use. Do not use if safety seal is broken or missing.

REFRIGERATE AFTER OPENING.
BEST WHEN USED WITHIN 30 DAYS OF OPENING.

QUESTIONS

Questions? Call 866.642.2858 Made with care by Uriel, East Troy, WI 53120 www.urielpharmacy.com